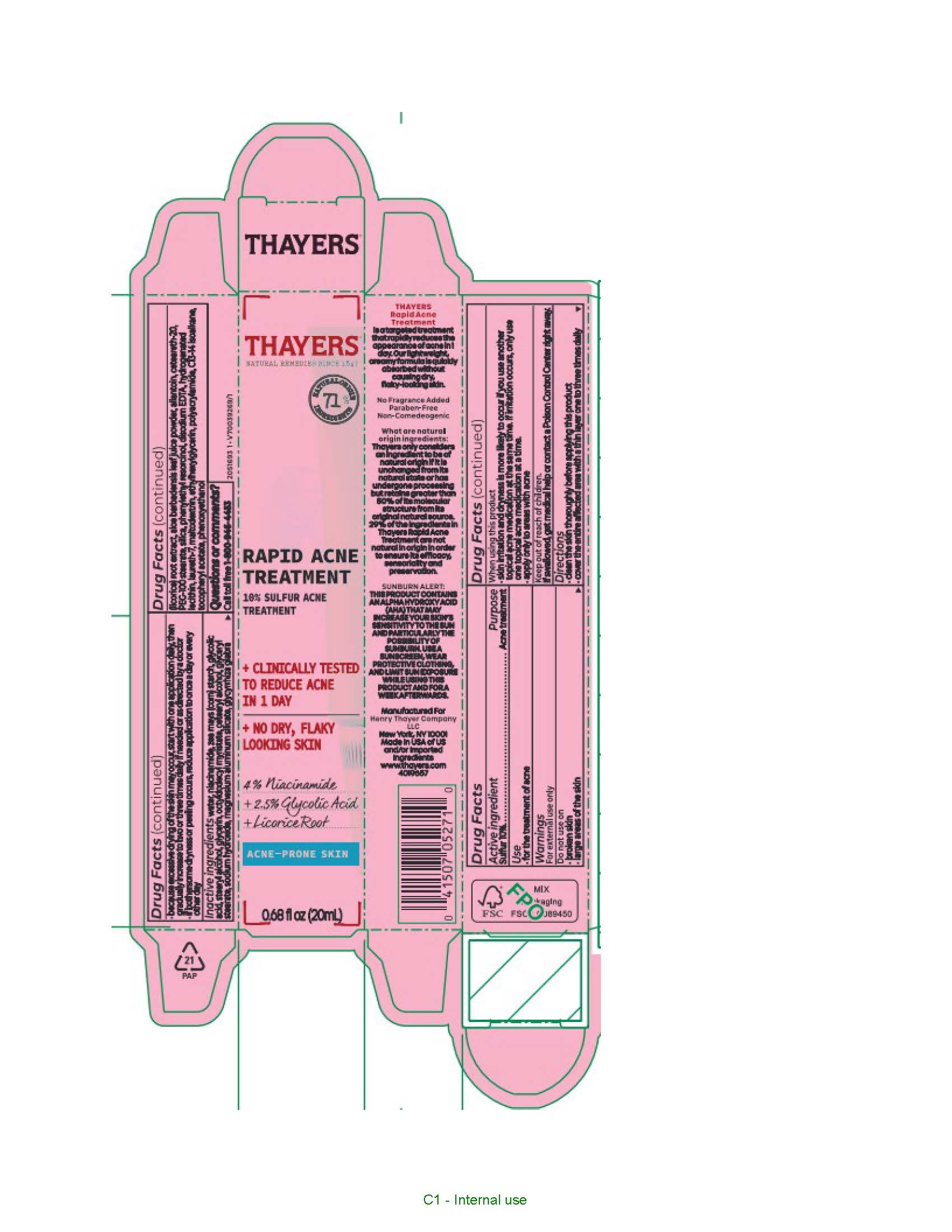 DRUG LABEL: Thayers Natural Remedies Since 1847 Rapid Acne Treatment
NDC: 49967-415 | Form: LOTION
Manufacturer: L'Oreal USA Products Inc
Category: otc | Type: HUMAN OTC DRUG LABEL
Date: 20240607

ACTIVE INGREDIENTS: SULFUR 100 mg/1 mL
INACTIVE INGREDIENTS: WATER; NIACINAMIDE; STARCH, CORN; GLYCOLIC ACID; STEARYL ALCOHOL; GLYCERIN; OCTYLDODECYL MYRISTATE; CETOSTEARYL ALCOHOL; GLYCERYL 1-STEARATE; SODIUM HYDROXIDE; MAGNESIUM ALUMINUM SILICATE; PHENOXYETHANOL; POLYACRYLAMIDE (10000 MW); POLYOXYL 20 CETOSTEARYL ETHER; PEG-100 STEARATE; .ALPHA.-TOCOPHEROL ACETATE; PHENYLETHYL RESORCINOL; C13-14 ISOPARAFFIN; EDETATE DISODIUM; LAURETH-7; ALLANTOIN; HYDROGENATED SOYBEAN LECITHIN; ETHYLHEXYLGLYCERIN; MALTODEXTRIN; GLYCYRRHIZA GLABRA; ALOE VERA LEAF; SILICON DIOXIDE

Drug Facts

Active ingredient

Sulfur 10%

Purpose

Acne treatment

Use

for the treatment of acne

Warnings

For external use only

Do not use on

- broken skin
- large areas of the skin

When using this product

- skin irritation and dryness is more likely to occur if you use another topical acne medication at the same time. If irritation occurs, only use one topical acne medication at a time.
- apply only to areas with acne

Keep out of reach of children.

If swallowed, get medical help or contact a Poison Control Center right away.

Directions

- clean the skin thoroughly before applying this product
- cover the entire affected area with a thin layer one to three times daily
- because excessive drying of the skin may occur, start with one application daily, then gradually increase to two or three times daily if needed or as directed by a doctor
- if bothersome dryness or peeling occurs, reduce application to once a day or every other day

Inactive ingredients

water, niacinamide, zea mays (corn) starch, glycolic acid, stearyl alcohol, glycerin, octyldodecyl myristate, cetearyl alcohol, glyceryl stearate, sodium hydroxide, magnesium aluminum silicate, phenoxyethanol, polyacrylamide, ceteareth-20, PEG-100 stearate, tocopheryl acetate, phenylethyl resorcinol, c13-14 isoalkane, disodium EDTA, laureth-7, allantoin, hydrogenated lecithin, ethylhexylglycerin, maltodextrin, glycyrrhiza glabra (licorice) root extract, aloe barbadensis leaf juice powder, silica

Questions or comments?

1-800-946-4453